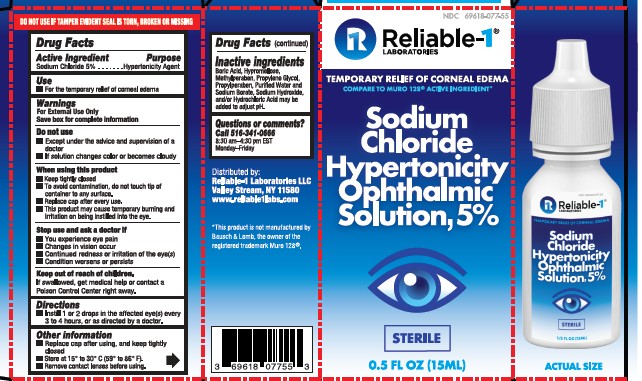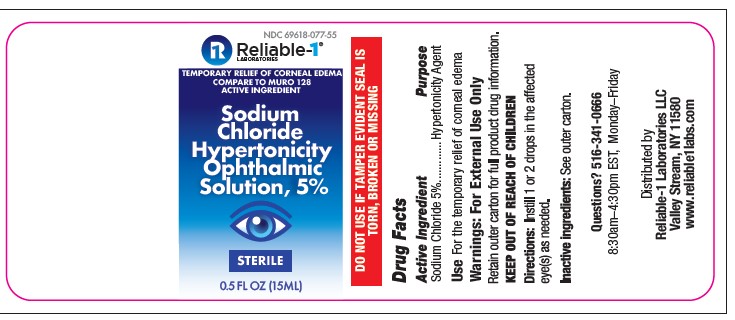 DRUG LABEL: Sodium Chloride Hypertonicity Ophthalmic Solution, 5%
NDC: 69618-077 | Form: SOLUTION/ DROPS
Manufacturer: Reliable 1 Laboritories LLC
Category: otc | Type: HUMAN OTC DRUG LABEL
Date: 20250115

ACTIVE INGREDIENTS: SODIUM CHLORIDE 50 mg/1 mL
INACTIVE INGREDIENTS: BORIC ACID; PROPYLPARABEN; SODIUM BORATE; SODIUM HYDROXIDE; HYPROMELLOSE, UNSPECIFIED; METHYLPARABEN; PROPYLENE GLYCOL; WATER; HYDROCHLORIC ACID

Sodium Chloride Hypertonicity Ophthalmic Solution, 5%

Active ingredient & purpose

DRUG FACTS

Active ingredient

Sodium chloride 5%

PURPOSE

Hypertonicity agent

USE

temporary relief of corneal edema

WARNINGS

For external use only

Save box for complete information

When using this product

- keep tightly closed
- to avoid contamination, do not touch tip of container to any surface
- replace cap after use
- this product may cause temporary burning and irritation on being instilled into the eye.

Stop use and ask a doctor if

- you experience eye pain
- changes in vision
- continued redness or irritation of the eye
- condition worsens or persists

Keep out of reach of children

If swallowed, get medical help or contact a Poison Control Center right away.

DIRECTIONS

Instill 1 or 2 drops in the affected eye(s) every 3 or 4 hours, or as directed by a doctor.

OTHER INFORMATION

- replace cap after using, and keep tightly closed
- store upright at 15–30 °C (59–86 °F)
- remove contact lenses before using

INACTIVE INGREDIENT

Boric Acid, Hypromellose Methylparaben, Propylene Glycol, Proplyparaben, purified water and sodium Borate, Sodium Hydroxide, and/or Hydrochloric Acid maybe added to adjust pH.

Questions or comments?

Call 1-516-341-0666

8:30AM-4:30PM

Monday – Friday

PACKAGE LABEL

NDC 696180-077-55

Reliable 1 Laboratories

Temporary relief of corneal edema

Compare to Muro 128® active ingredient*

Sodium Chloride Hypertonicity Ophthalmic Solution, 5%

Sterile

0.5 fl oz (15mL)

*This product is not manufactured by Bausch & Lomb, the owner of the registered trademark Muro 128®

Distributed by

Reliable 1 Laboratories LLC

Valley Stream, NY 11580

Reliable1labs.com